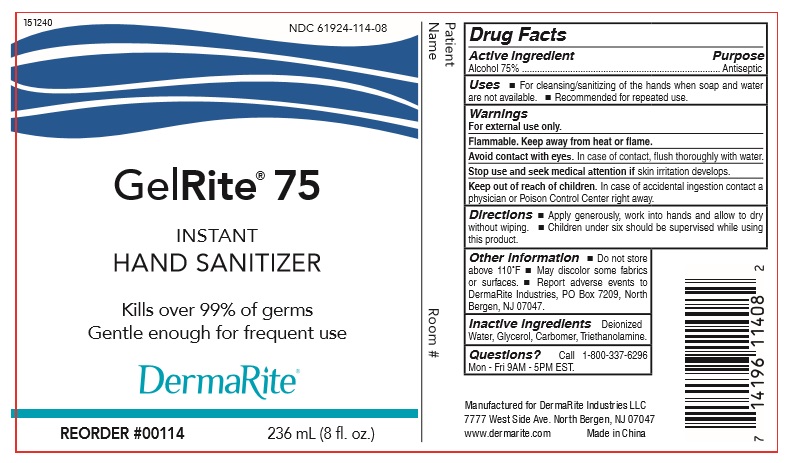 DRUG LABEL: Hand Sanitizer
NDC: 61924-114 | Form: GEL
Manufacturer: DERMARITE INDUSTRIES, LLC
Category: otc | Type: HUMAN OTC DRUG LABEL
Date: 20220113

ACTIVE INGREDIENTS: ALCOHOL 75 mL/100 mL
INACTIVE INGREDIENTS: TROLAMINE; GLYCERIN; WATER; CARBOMER 934

GELRITE 75

Active Ingredient(s)

Ethyl Alcohol 75% Purpose: Antiseptic

Purpose

Antiseptic, Hand Sanitizer

Use

For cleansing/sanitizing of the hands when soap and water are not available.

Recommended for repeated use.

Warnings

For external use only. Flammable. Keep away from heat or flame. Avoid contact with eyes. In case of contact, flush thoroughly with water. Stop use and seek medical attention if skin irritation develops.

Stop use and ask a doctor if irritation or rash occurs. These may be signs of a serious condition.

Keep out of reach of children. In case of accidental ingestion contact a physician or Poison Control Center right away.

Directions

Apply Generously, work into hands and allow to dry without wiping.

Children under six should be supervised while using this product.

Other information

- Do not store above 110F
- May discolor some fabrics or surfaces.
- Report adverse events to DermaRite Industries, PO box 7209, North Bergen, NJ 07047

Inactive ingredients

Deionized Water, glycerol, Carbomer, Triethanolamine

Questions?

Call 1-800-337-6296

Mon-Fri 9AM- 5PM EST.

Package Label - Principal Display Panel

8 oz NDC: 61924-114-08